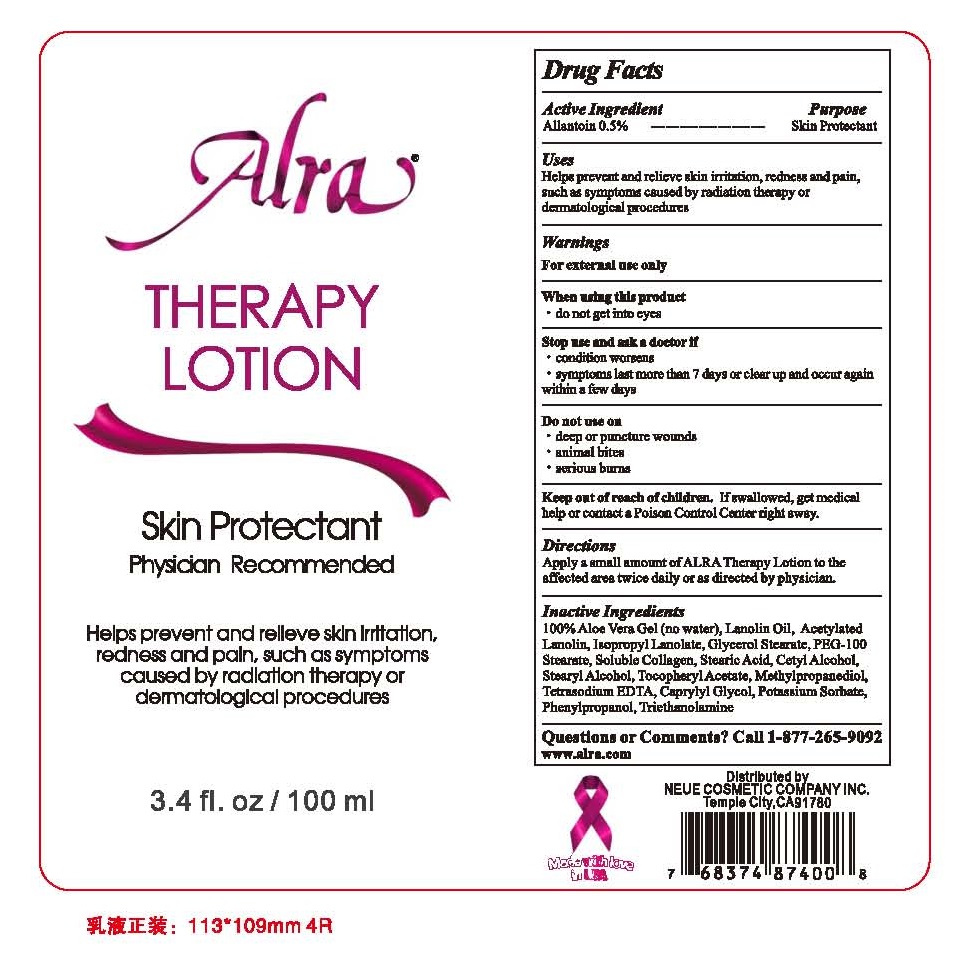 DRUG LABEL: ALRA THERAPY
NDC: 58894-101 | Form: LOTION
Manufacturer: NEUE COSMETIC COMPANY INC
Category: otc | Type: HUMAN OTC DRUG LABEL
Date: 20160614

ACTIVE INGREDIENTS: ALLANTOIN 0.5 g/100 mL
INACTIVE INGREDIENTS: ALOE VERA LEAF; LANOLIN OIL; ACETYLATED LANOLIN; ISOPROPYL LINOLEATE; GLYCERYL MONOSTEARATE; PEG-100 STEARATE; MARINE COLLAGEN, SOLUBLE; STEARIC ACID; CETYL ALCOHOL; STEARYL ALCOHOL; .ALPHA.-TOCOPHEROL ACETATE; METHYLPROPANEDIOL; EDETATE SODIUM; CAPRYLYL GLYCOL; POTASSIUM SORBATE; PHENYLPROPANOL; TROLAMINE

ACTIVE INGREDIENTS

ALLANTOIN 0.5%

PURPOSE

SKIN PROTECTANT

USES

HELPS PREVENT AND RELIEVE SKIN IRRITATION, REDNESS AND PAIN, SUCH AS SYMPTOMS CAUSED BY RADIATION THERAPY OR DERMATOLOGICAL PROCEDURES.

WARNINGS

FOR EXTERNAL USE ONLY

WHEN USING THIS PRODUCT

- DO NOT GET INTO EYES

STOP USE AND ASK A DOCTOR IF

- CONDITIONS WORSEN
- SYMPTOMS LAST MORE THAN 7 DAYS OR CLEAR UP AND OCCUR AGAIN WITHIN A FEW DAYS

DO NOT USE ON

- DEEP OR PUNCTURE WOUNDS
- ANIMAL BITES
- SERIOUS BURNS

KEEP OUT OF REACH OF CHILDREN. IF SWALLOWED, GET MEDICAL HELP OR CONTACT A POISON CONTROL CENTER RIGHT AWAY.

DIRECTIONS

APPLY A SMALL AMOUNT OF ALRA THERAPY LOTION TO THE AFFECTED AREA TWICE DAILY OR AS DIRECTED BY PHYSICIAN.

INACTIVE INGREDIENTS

100% ALOE VERA (NO WATER), LANOLIN OIL, ACETYLATED LANOLIN, ISOPROPYL LANOLATE, GLYCEROL STEARATE, PEG-100 STEARATE, SOLUBLE COLLAGEN, STEARIC ACID, CETYL ALCOHOL, STEARYL ALCOHOL, TOCOPHERYL ACETATE, METHYLPROPANEDIOL, TETRASODIUM EDTA, CAPRYLYL GLYCOL, POTASSIUM SORBATE, PHENYLPROPANOL, TRIETHANOLAMINE

QUESTIONS OR COMMENTS?

CALL 1-877-265-9092

WWW.ALRA.COM